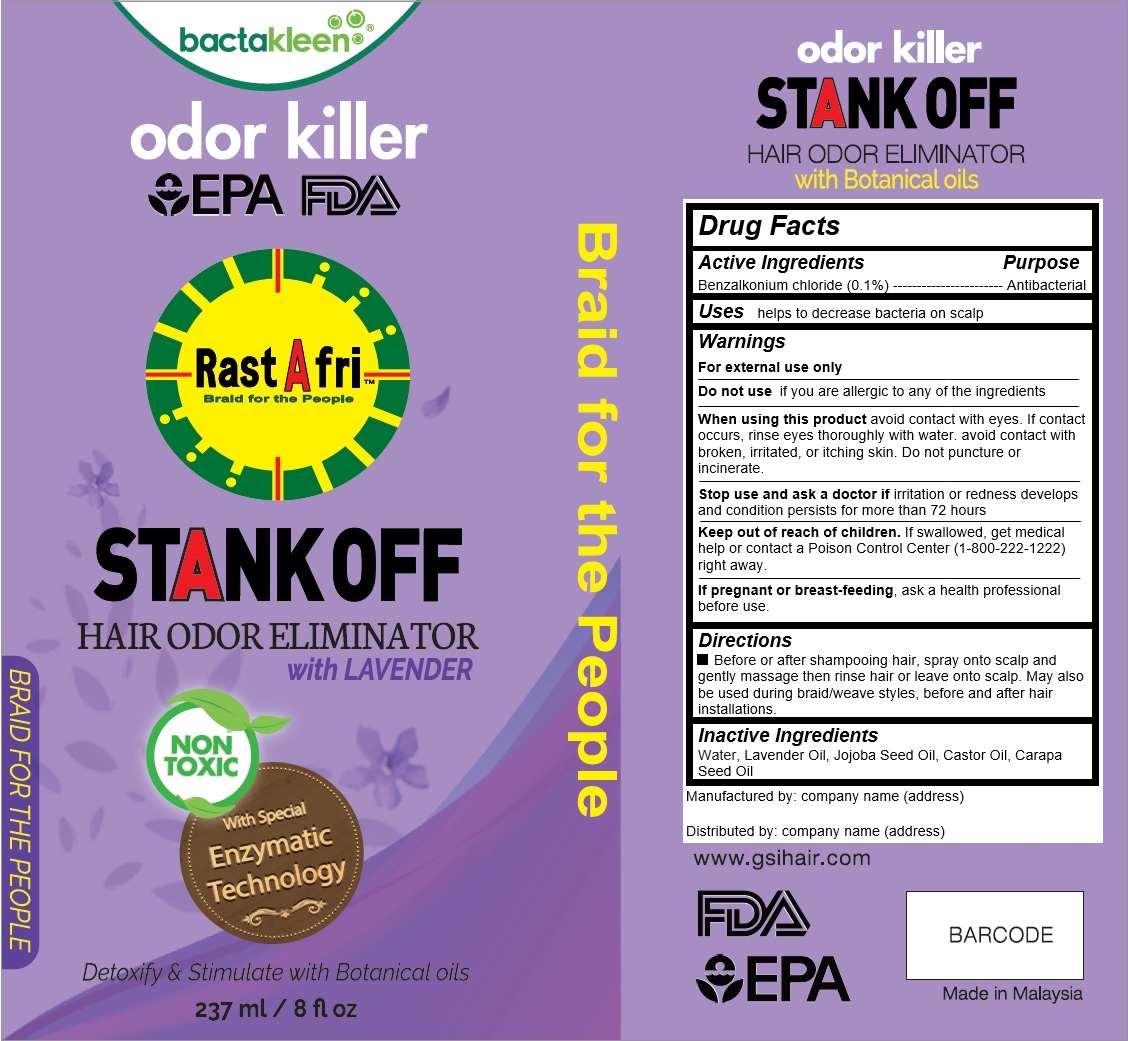 DRUG LABEL: Rast A Fri Stank Off Odor Eliminator Lavender
NDC: 73249-103 | Form: LIQUID
Manufacturer: GS Imports, Inc.
Category: otc | Type: HUMAN OTC DRUG LABEL
Date: 20190812

ACTIVE INGREDIENTS: BENZALKONIUM CHLORIDE 0.237 g/237 mL
INACTIVE INGREDIENTS: WATER

Rast A Fri Stank Off Odor Eliminator Lavender

Active Ingredients

Benzalkonium chloride (0.1%)

Purpose

Antibacterial

Keep out of reach of children

If swallowed, get medical help or contact a Poison Control Center (1-800-222-1222) right away.

Uses

helps to decrease bacteria on scalp

Warnings

For external use only

Do not use if you are allergic to any of the ingredients

When using this product avoid contact with eyes. If contact occurs, rinse eyes thoroughly with water. avoid contact with broken, irritated, or itching skin. Do not puncture or incinerate.

Stop use and ask a doctor if irritation or redness develops and condition persists for more than 72 hours

If pregnant or breast-feeding, ask a health professional before use.

DOSAGE AND ADMINISTRATION

Before or after shampooing hair, spray onto scalp and gently massage then rinse hair or leave onto scalp. May also be used during braid/weave styles, before and after hair installations.

Inactive Ingredients

Water, Lavender Oil, Jojoba Seed Oil, Castor Oil, Carapa Seed Oil